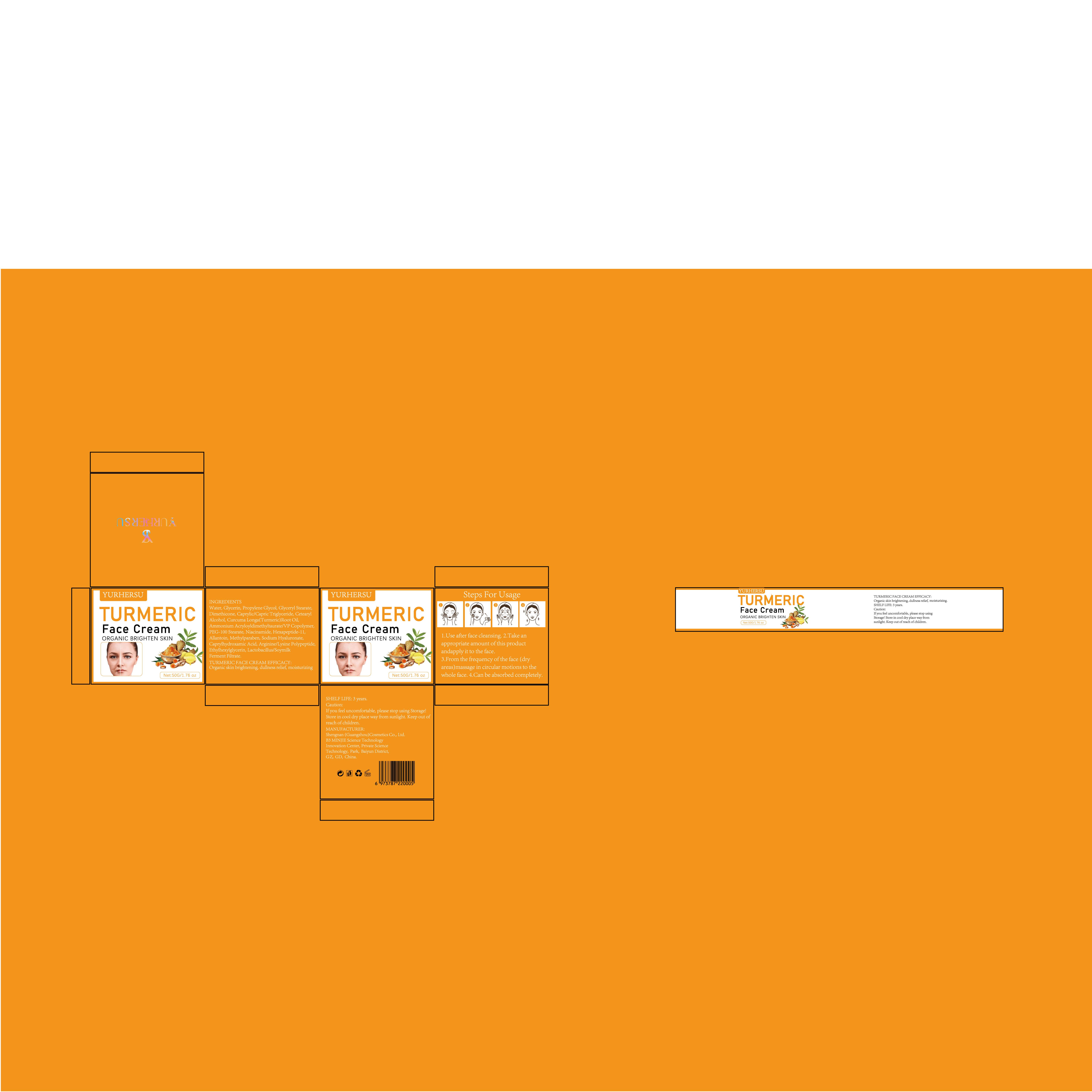 DRUG LABEL: TURMERICFaceCream
NDC: 84019-025 | Form: CREAM
Manufacturer: Shengnan (Guangzhou) Cosmetics Co., LTD
Category: otc | Type: HUMAN OTC DRUG LABEL
Date: 20250106

ACTIVE INGREDIENTS: NIACINAMIDE 100 mg/1 g
INACTIVE INGREDIENTS: GLYCERIN; SODIUM HYALURONATE; CAPRYLIC/CAPRIC TRIGLYCERIDE; ALLANTOIN; WATER; GLYCERYL STEARATE; PEG-100 STEARATE; HEXAPEPTIDE-11; CAPRYLHYDROXAMIC ACID; DIMETHICONE; CETEARYL ALCOHOL

WARNINGS

Please keep out of reach of children.

PURPOSE

Organic skin brightening, dullness relief, moisturizing

STOP USE

This product is only applied to the surface of the skin and can not be taken orally, lf you feel unwell, please stop using immediately.

ACTIVE INGREDIENT

Niacinamide

WHEN USING

Please clean your skin before use to ensure the product works best.

INACTIVE INGREDIENT

Water
Glycerin
Propylene Glycol
Glyceryl Stearate
Dimethicone
Caprylic/Capric Triglyceride
Cetearyl Alcohol
Curcuma Longa(Turmeric)Root Oil
Ammonium Acryloyldimethyltaurate/VP Copolymer
PEG-100 Stearate
Hexapeptide-11
Allantoin
Methylparaben
Sodium Hyaluronate
Caprylhydroxamic Acid
Arginine/Lysine Polypeptide
Ethylhexylglycerin
Lactobacillus/Soymilk Ferment Filtrate

DOSAGE AND ADMINISTRATION

Apply 1 times a day

INDICATIONS AND USAGE

1.Use after face cleansing. 2.Take anappropriate amount of this productandapply it to the face.3.From the frequency of the face (dryareas)massage in circular motions to thewhole face. 4.Can be absorbed completely.